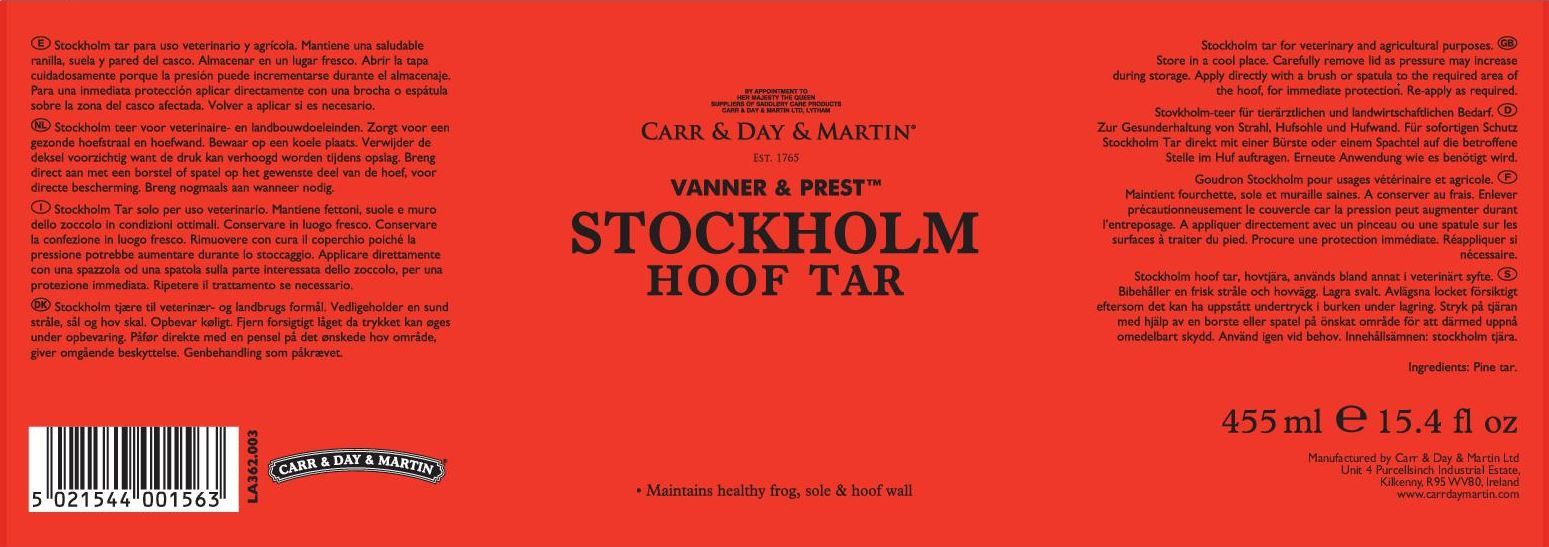 DRUG LABEL: Stockholm Hoof Tar
NDC: 43258-300 | Form: SALVE
Manufacturer: Carr & Day & Martin Unlimited Company
Category: animal | Type: OTC ANIMAL DRUG LABEL
Date: 20241219

ACTIVE INGREDIENTS: PINE TAR 1000 g/1 L

CARR & DAY & MARTIN®
VANNER & PREST
STOCKHOLM HOOF TAR

INDICATIONS AND USAGE

Stockholm tar for veterinary and agricultural purposes.

- Maintains healthy frog, sole, and hoof wall

GENERAL PRECAUTIONS

Store in a cool dry place.

Carefully remove lid as pressure may increase during storage.

DOSAGE AND ADMINISTRATION

Apply directly with a brush or spatula to the required area of the hoof, for immediate protection. Re-apply as required.

Manufactured by Carr & Day & Martin Unlimited Company

Unit 4 Purcellsinch Industrial Estate

Kilkenny, R95 WV80, Ireland

www.carrdaymartin.com